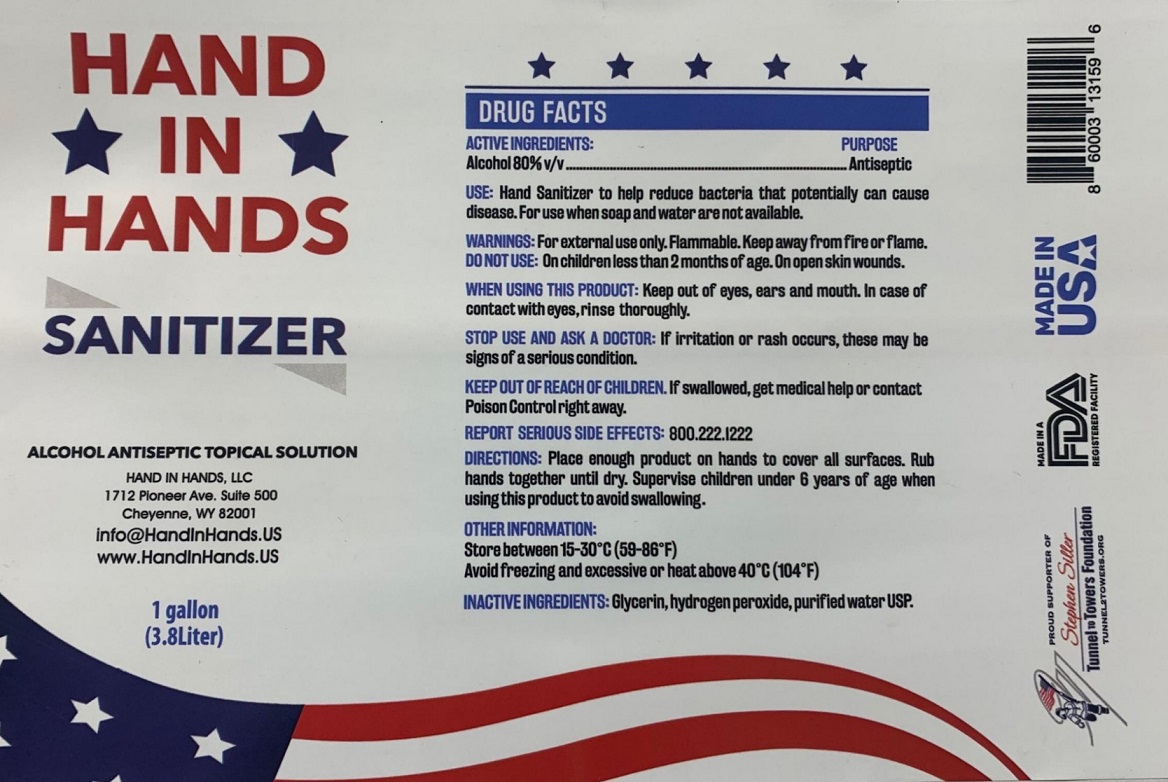 DRUG LABEL: Hand In Hands Sanitizer
NDC: 77778-001 | Form: SOLUTION
Manufacturer: Hand In Hands, Llc
Category: otc | Type: HUMAN OTC DRUG LABEL
Date: 20200605

ACTIVE INGREDIENTS: ALCOHOL 0.8 L/1 L
INACTIVE INGREDIENTS: GLYCERIN; HYDROGEN PEROXIDE; WATER

HAND IN HANDS SANITIZER

ACTIVE INGREDIENTS:

Alcohol 80% v/v

PURPOSE

Antiseptic

INDICATIONS AND USAGE

USE: Hand Sanitizer to help reduce bacteria that potentially can cause disease. For use when soap and water are not available.

WARNINGS

WARNINGS: For external use only. Flammable, Keep away from fire or flame.

DO NOT USE: On children less than 2 months of age. On open skin wounds.

WHEN USING THIS PRODUCT: Keep out of eyes, ears and mouth. In case of contact with eyes, rinse thoroughly.

STOP USE AND ASK A DOCTOR: If irritation or rash occurs, these may be signs of a serious condition.

KEEP OUT OF REACH OF CHILDREN. If swallowed, get medical help or contact a Poison Control right away.

QUESTIONS

REPORT SERIOUS SIDE EFFECTS: 800.222.1222

DOSAGE AND ADMINISTRATION

DIRECTIONS: Place enough product on hands to cover all surfaces. Rub hands together until dry. Supervise children under 6 years

of age when using this product to avoid swallowing.

OTHER INFORMATION:

Store between 15-30°C (59-86°F)

Avoid freezing and excessive or heat above 40°C (104°F)

INACTIVE INGREDIENTS: Glycerin, hydrogen peroxide, purified water USP.

ALCOHOL ANTISEPTIC TOPICAL SOLUTION

HAND IN HANDS, LLC

1712 Pioneer Ave. Suite 500

Cheyenne, WY 82001

info@HandInHands.US

WWW.HandInHands.US

PROUD SUPPORTER OF

Stephen Siller

Tunnel To Towers Foundation

TUNNEL2TOWERS.ORG

MADE IN A FDA REGISTERED FACILITY

MADE IN USA